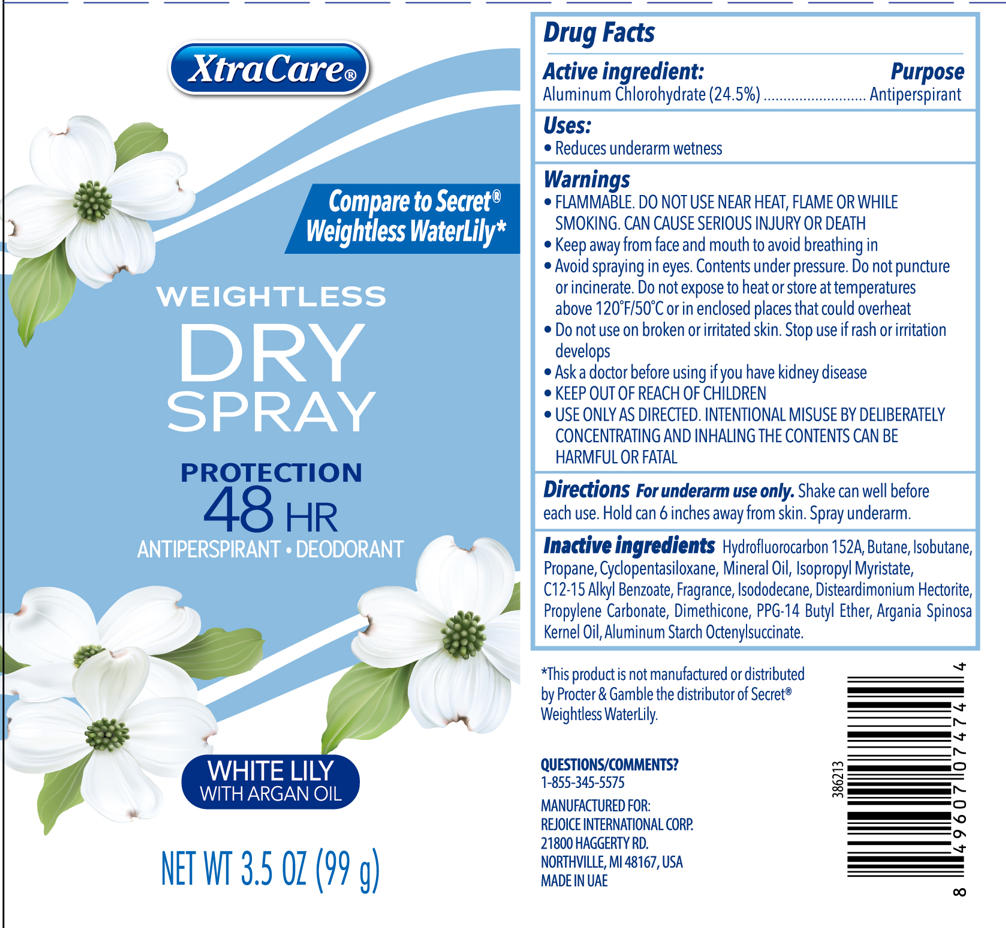 DRUG LABEL: 3.5OZ WOMENS DRY WHITE LILY
NDC: 57337-183 | Form: SPRAY
Manufacturer: Rejoice International Corp.
Category: otc | Type: HUMAN OTC DRUG LABEL
Date: 20250923

ACTIVE INGREDIENTS: ALUMINUM CHLOROHYDRATE 24.5 g/100 g
INACTIVE INGREDIENTS: ISOBUTANE; ISODODECANE; PPG-14 BUTYL ETHER; CYCLOPENTASILOXANE; PROPANE; C12-15 ALKYL BENZOATE; DISTEARDIMONIUM HECTORITE; PROPYLENE CARBONATE; BUTANE; MINERAL OIL; ARGANIA SPINOSA KERNEL OIL; ISOPROPYL MYRISTATE; HYDROFLUOROCARBON 152A; DIMETHICONE; ALUMINUM STARCH OCTENYLSUCCINATE

3.5OZ WOMEN'S DRY SPRAY WHITE LILY

Active ingredient

Aluminum Chlorohydrate 24.5%

Purpose

Antiperspirant

Uses

Reduces underarm wetness

Warnings

- FLAMMABLE. DO NOT USE NEAR HEAT, FLAME OR WHILE SMOKING. CAN CAUSE SERIOUS INJURY OR DEATH.
- Keep away from face and mouth to avoid breathing in
- Avoid spraying in eyes. Contents under pressure. Do not puncture or incinerate. Do not expose to heat or store at temperatures above 120F/50 C or in enclosed places that could overheat.

Do not use on broken or irritated skin. Stop use if rash or irritation develops

Ask a doctor before using if you have kidney disease

Keep out of reach of children

Use only as directed

INTENTIONAL MISUSE BY DELIBERATELY CONCENTRATING AND INHANLING THE CONTENTS CAN BE HARMFUL OR FATAL

Directions

For underarm use only.

Shake can well before each use. Hold can 6 inches away from skin. Spray underarm.

Inactive ingredients

Hydrofluorocarbon 152A

Butane

Isobutane

Propane

Cyclopentasiloxane

Mineral Oil

Isopropyl Myristate

C12-15 Alkyl Benzoate

Fragrance

Isododecane

Disteardimonium Hectorite

Propylene Carbonate

Dimethicone

PPG-14 Butyl Ether

Argania Spinosa Kernel Oil

Aluminum Starch Octenylsuccinate